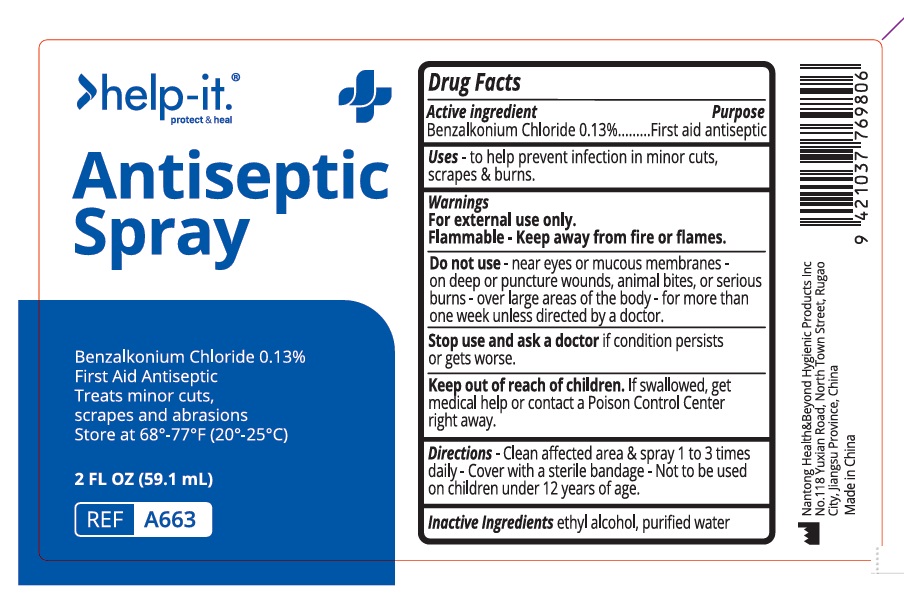 DRUG LABEL: help it Antiseptic
NDC: 43473-078 | Form: SPRAY
Manufacturer: Nantong Health & Beyond Hygienic Products Inc.
Category: otc | Type: HUMAN OTC DRUG LABEL
Date: 20250527

ACTIVE INGREDIENTS: BENZALKONIUM CHLORIDE 0.13 g/100 mL
INACTIVE INGREDIENTS: WATER; ALCOHOL

43473-078 Antiseptic Spray

Active ingredient

BENZALKONIUM CHLORIDE 0.13%

Purpose

Fist Aid Antiseptic

Uses

To help prevent infection in minor cuts, scrapes, and burns

Warnings

For external use only.

Flammable: keep away from fire or flames

Do not use

- near eyes or mucous membranes
- on deep or puncture wounds, animal bites, or serious burns
- over large areas of the body
- for more than one week unless directed by a doctor

Stop use and ask a doctor if condition persists or get worse

Keep out of reach of children. If swallowed, get medical help or contact a Poison Control Center right away.

Directions:

- Clean affected area and spray 1-3 times daily
- Cover with a sterile bandage
- Not to be used on children under 12 years of age

Inactive ingredients

ethyl alcohol, purified water